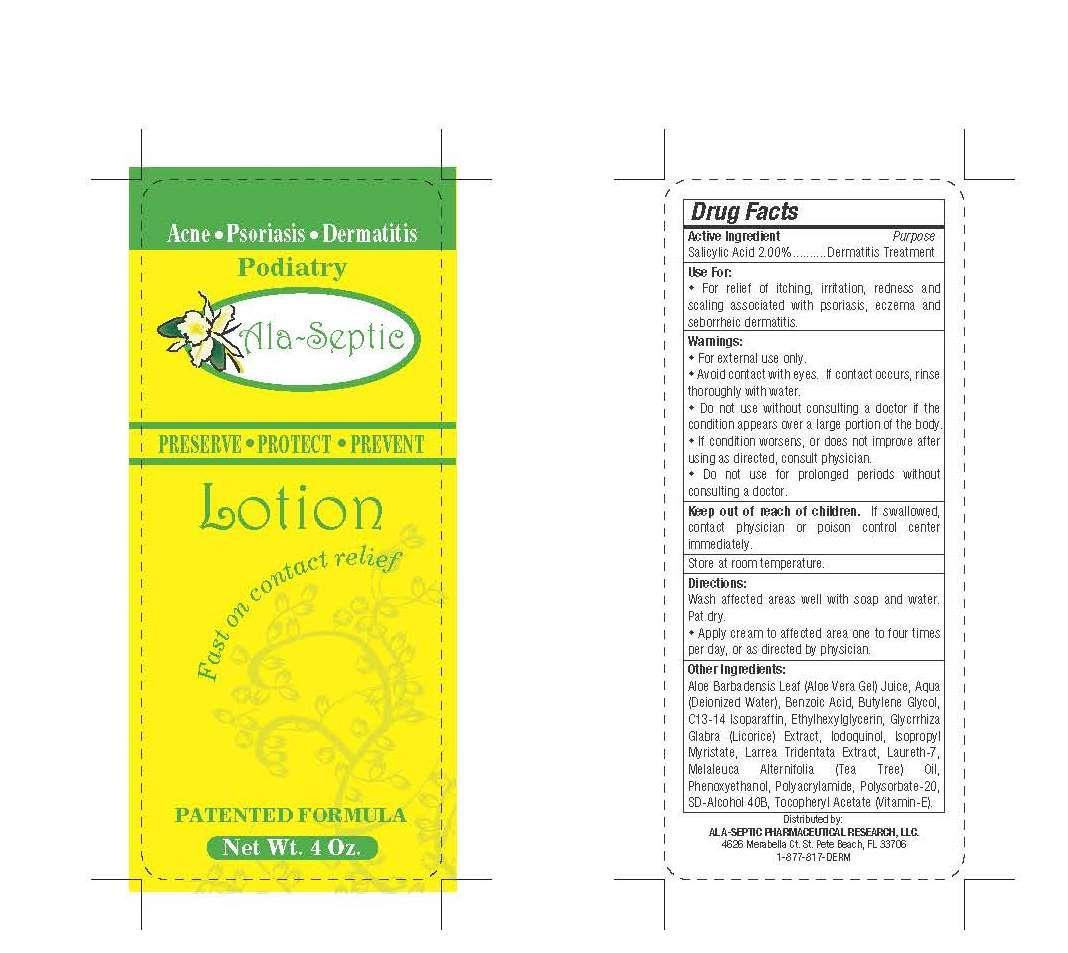 DRUG LABEL: Ala-Septic
NDC: 59434-001 | Form: CREAM
Manufacturer: Ala-Septic Pharmaceutical Research LLC
Category: otc | Type: HUMAN OTC DRUG LABEL
Date: 20131216

ACTIVE INGREDIENTS: SALICYLIC ACID 2 g/100 g
INACTIVE INGREDIENTS: ALOE VERA WHOLE; water; BENZOIC ACID; BUTYLENE GLYCOL; C13-14 ISOPARAFFIN; ETHYLHEXYLGLYCERIN; LICORICE; IODOQUINOL; ISOPROPYL MYRISTATE; LARREA TRIDENTATA WHOLE; LAURETH-7; TEA TREE OIL; PHENOXYETHANOL; POLYACRYLAMIDE (10000 MW); POLYSORBATE 20; ALCOHOL; .ALPHA.-TOCOPHEROL ACETATE

Ala-Septic

warnings

For external use only.

Avoid contact with eyes. If contact occurs, rinse thoroughly with water.

Do not use without consulting a doctor if the condition appears over a large portion of hte body.

If condition worsens, or does not improve after using as directed, consult physician.

Do not use for prolonged periods without consulting a docotor.

Active ingredient

Salicylic Acid 2.00%

Purpose

Dermatitis Treatment

Use for:

For relief of itching, irritation, redness and scaling assoicated with psoriasis, eczema and seborrheic dermatitis.

Other ingredients:

Aloe Barbadensis Leaf Juice, Aqua (deionized water), benzoic acid, butylene glycol, C13-14 isoparaffin, ethylhexylglycerin, glycrrhiza glabra (licorice) extract, iodoquinol, isoproply myristate, larrea tridentata extract, larueth-7, melaleuca alternifolia (tea tree) oil, phenoxyethanol, polyacrylamide, polysorbate-20, SD-alcohocl 40B, tocopheryl acetate (vitamin E).

Keep out of reach of children.

If swallowed, contact physician or poison control center immediately.

Directions:

Wash affected areas well with soap and water. Pat dry. Apply cream to affected area one to four times per day, or as directed by physician.